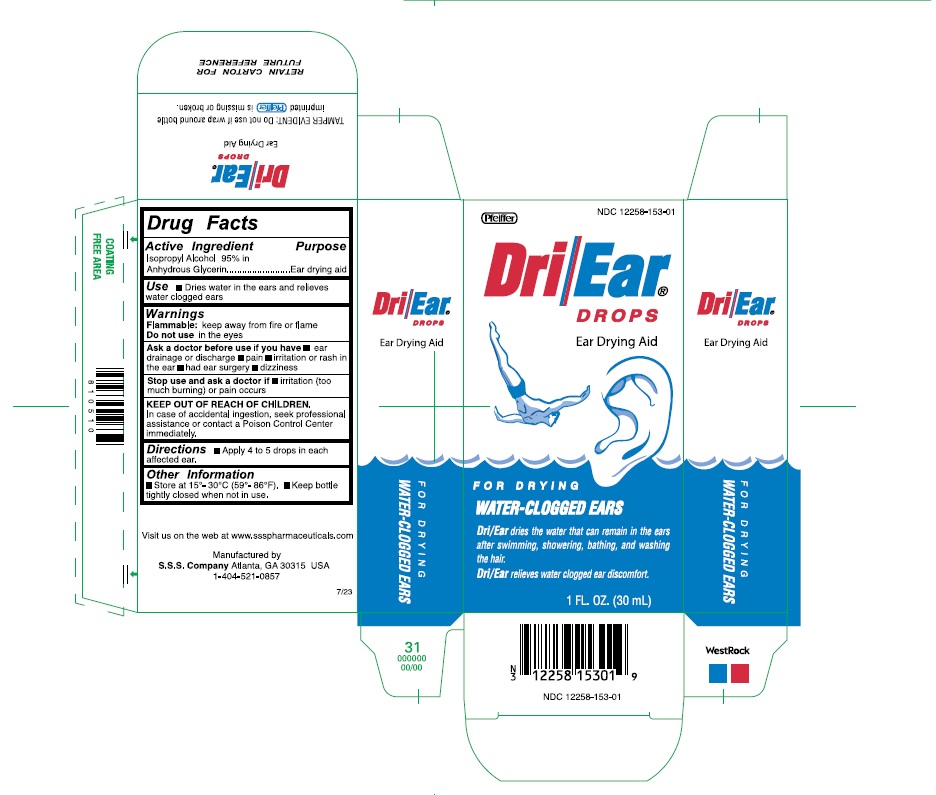 DRUG LABEL: Dri-Ear
NDC: 12258-153 | Form: SUSPENSION/ DROPS
Manufacturer: S.S.S. Company
Category: otc | Type: HUMAN OTC DRUG LABEL
Date: 20260108

ACTIVE INGREDIENTS: ISOPROPYL ALCOHOL 950 mg/1 mL
INACTIVE INGREDIENTS: GLYCERIN

Doasge and Administration.

Apply 4 to 5 drops in each affected ear

Warnings

Flammable: keep away from fire or flame
Do not us e in the eyes

Inactive Ingredient

Glycerin

Indication

Dries water in the ears and relieves water clogged ears

KEEP OUT OF REACH OF CHILDREN

In case of accidental ingestion , seek professional assistance or contact a Poison Control Center immediately.

Purpose

Ear Drying Aid